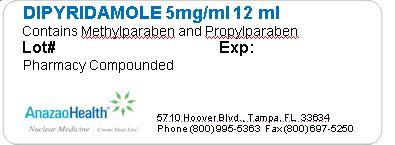 DRUG LABEL: Dipyridamole
NDC: 51808-204 | Form: SOLUTION
Manufacturer: AnazaoHealth Corporation
Category: prescription | Type: HUMAN PRESCRIPTION DRUG LABEL
Date: 20120523

ACTIVE INGREDIENTS: DIPYRIDAMOLE 5 mg/1 mL
INACTIVE INGREDIENTS: METHYLPARABEN; PROPYLPARABEN

DIPYRIDAMOLE

Dear Medical Professional,

Per your order, we have compounded Dipyridamole as 12 mL in a 10 mL vial. The characteristics of this preparation are described below

DESCRIPTION

AnazaoHealth’s compounded Dipyridamole vial is a sterile, non-pyrogenic preparation that is 5mg/mL. This vial contains no antimicrobial preservative

INDICATIONS AND USAGE

Dipyridamole is a coronary vasodilator and is indicated as an alternative to exercise in thallium myocardial perfusion imaging for the evaluation of coronary artery disease in patients who cannot exercise adequately

DOSAGE AND ADMINISTRATION

The recommended dose is 0.142 mg/kg/minute (0.57 mg/kg total) or 0.568 mg/kg or 60 mg total dose infused over 4 minutes. Although the maximum tolerated dose has not been determined, clinical experience suggests that a total dose beyond 60 mg is not needed for any patient.

Prior to intravenous administration, dipyridamole should be diluted in at least a 1:2 ratio with 0.45% sodium chloride injection, 0.9% sodium chloride injection, or 5% dextrose injection for a total volume of approximately 20 to 50 mL. Infusion of undiluted dipyridamole injection may cause local irritation.

Myocardial perfusion assessment should be started when maximal vasodilation is reached, usually after 3 minutes, which generally occurs approximately 7 minutes from onset of infusion

ADVERSE REACTIONS

Flushing, chest pain, dyspnea, headache, dizziness, nausea, vomiting, palpitations, arm/back/shoulder pain, arrhythmias, paresthesias, pulmonary edema, asystole myocardial infarcation

Side effects can be easily reversed by an administration of an IV bolus of 50-75 mg of Aminophylline or an infusion of 250-500 mg over 20 minutes

CONTRAINDICATIONS

Theophylline therapy, active wheezing, high grade antroventricular block

Storage and Handling

Dipyridamole should be stored at room temperature and protected from light.

PACKAGE LABEL.PRINCIPAL DISPLAY PANEL

Figure 1